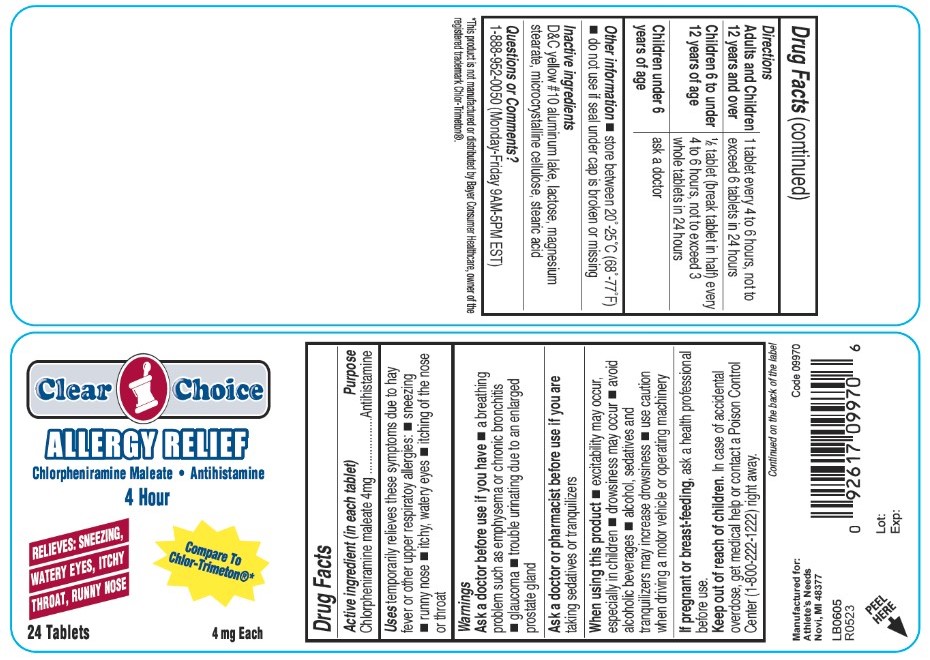 DRUG LABEL: Chlorpheniramine maleate 4mg
NDC: 53185-277 | Form: TABLET, COATED
Manufacturer: Athlete's Needs, Inc.
Category: otc | Type: HUMAN OTC DRUG LABEL
Date: 20171114

ACTIVE INGREDIENTS: CHLORPHENIRAMINE MALEATE 4 mg/1 1
INACTIVE INGREDIENTS: D&C YELLOW NO. 10; LACTOSE, UNSPECIFIED FORM; MAGNESIUM STEARATE; MICROCRYSTALLINE CELLULOSE; STEARIC ACID

Allergy Relief 4 Hour

Active ingredient (in each tablet)

Chlorpheniramine maleate 4mg

Purpose

Antihistamine

Uses

temporarily relieves these symptoms due to hay fever or other upper respiratory allergies:

- sneezing
- runny nose
- itchy, watery eyes
- itching of the nose or throat

Warnings

Ask a doctor before use if you have

- a breathing problem such as emphysema or chronic bronchitis
- glaucoma
- trouble urinating due to an enlarged prostate gland

Ask a doctor or pharmacist before use if you are

taking sedatives or tranquilizers

When using this product

- excitability may occur, especially in children
- drowsiness may occur
- avoid alcoholic beverages
- alcohol, sedatives and tranquilizers may increase drowsiness
- use caution when driving a motor vehicle or operating machinery

If pregnant or breast-feeding,

ask a health professional before use.

Keep out of reach of children.

In case of accidental overdose, get medical help or contact a Poison Control Center (1-800-222-1222) right away.

Directions

- Adults and children 12 years and over: 1 tablet every 4 to 6 hours, not to exceed 6 tablets in 24 hours
- Children 6 to under 12 years of age: &frac12; tablet (break tablet in half) every 4 to 6 hours, not to exceed 3 whole tablets in 24 hours
- Children under 6 years of age: ask a doctor

Other information

- store between 20°-25°C (68°-77°F)
- do not use if seal under cap is broken or missing

Inactive ingredients

D&C yellow #10 aluminum lake, lactose, magnesium stearate, microcrystalline cellulose, stearic acid

Questions or Comments?

1-888-952-0050 (Monday-Friday 9AM-5PM EST)

Principal Display Panel

Allergy Relief